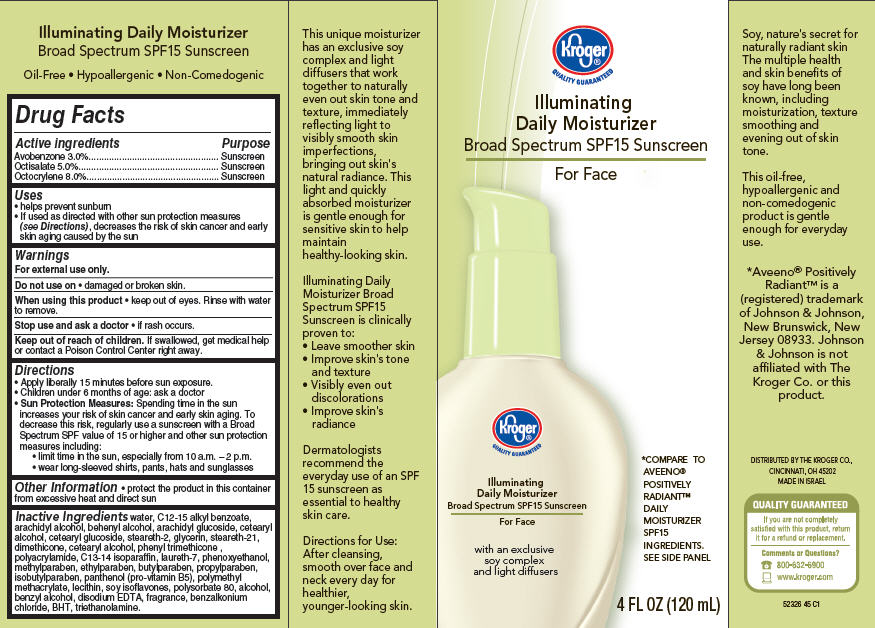 DRUG LABEL: Illuminating Daily Moisturizer
NDC: 30142-705 | Form: CREAM
Manufacturer: The Kroger Co.
Category: otc | Type: HUMAN OTC DRUG LABEL
Date: 20120517

ACTIVE INGREDIENTS: AVOBENZONE 3 mL/100 mL; OCTISALATE 5 mL/100 mL; OCTOCRYLENE 8 mL/100 mL
INACTIVE INGREDIENTS: WATER; ALKYL (C12-15) BENZOATE; ARACHIDYL ALCOHOL; DOCOSANOL; ARACHIDYL GLUCOSIDE; CETOSTEARYL ALCOHOL; CETEARYL GLUCOSIDE; STEARETH-2; GLYCERIN; STEARETH-21; DIMETHICONE; PHENYL TRIMETHICONE; POLYACRYLAMIDE (10000 MW); C13-14 ISOPARAFFIN; LAURETH-7; PHENOXYETHANOL; METHYLPARABEN; ETHYLPARABEN; BUTYLPARABEN; PROPYLPARABEN; ISOBUTYLPARABEN; PANTHENOL; POLY(METHYL ACRYLATE-CO-METHYL METHACRYLATE-CO-METHACRYLIC ACID 7:3:1; 280000 MW); LECITHIN, SOYBEAN; SOY ISOFLAVONES; POLYSORBATE 80; ALCOHOL; BENZYL ALCOHOL; EDETATE DISODIUM; BENZALKONIUM CHLORIDE; BUTYLATED HYDROXYTOLUENE; TROLAMINE

Kroger® Illuminating Daily Moisturizer Broad Spectrum SPF15 Sunscreen for Face

Active ingredient

Avobenzone 3.0%
Octisalate 5.0%
Octocrylene 8.0%

Purpose

Sunscreen

Uses

- helps prevent sunburn
- If used as directed with other sun protection measures (see Directions), decreases the risk of skin cancer and early skin aging caused by the sun

Warnings

For external use only.

Do not use on

- damaged or broken skin.

When using this product

- keep out of eyes. Rinse with water to remove.

Stop use and ask a doctor

- if rash occurs.

Keep Out of Reach of Children.

If swallowed, get medical help or contact a Poison Control Center right away.

Directions

- Apply liberally 15 minutes before sun exposure.
- Children under 6 months of age: ask a doctor
- Sun Protection Measures: Spending time in the sun increases your risk of skin cancer and early skin aging. To decrease this risk, regularly use a sunscreen with a Broad Spectrum SPF value of 15 or higher and other sun protection measures including:
  - limit time in the sun, especially from 10 a.m. - 2 p.m.
  - wear long-sleeved shirts, pants, hats and sunglasses

Other Information

- protect the product in this container from excessive heat and direct sun

Inactive ingredients

water, C12-15 alkyl benzoate, arachidyl alcohol, behenyl alcohol, arachidyl glucoside, cetearyl alcohol, cetearyl glucoside, steareth-2, glycerin, steareth-21, dimethicone, cetearyl alcohol, phenyl trimethicone, polyacrylamide, C13-14 isoparaffin, laureth-7, phenoxyethanol, methylparaben, ethylparaben, butylparaben, propylparaben, isobutylparaben, panthenol (pro-vitamin B5), polymethyl methacrylate, lecithin, soy isoflavones, polysorbate 80, alcohol, benzyl alcohol, disodium EDTA, fragrance, benzalkonium chloride, BHT, triethanolamine

Package/Label Principal Display Panel

Kroger® Illuminating Daily Moisturizer
Broad Spectrum SPF15 Sunscreen For Face

Quality Guaranteed

With an exclusive soy complex and light diffusers

*compare to Aveeno® Positively RadiantTM Daily Moisturizer SPF15 Ingredients, See Side Panel

4 FL OZ (120 mL)

DISTRIBUTED BY THE KROGER CO.,
CINCINNATI, OH 45202

Made in Israel
52326 45 C1

Carton Label